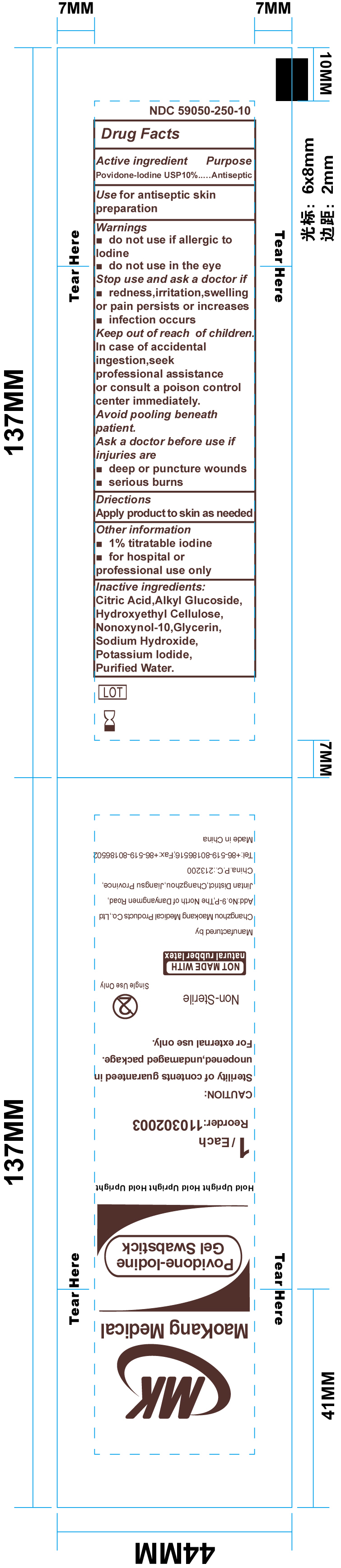 DRUG LABEL: Povidone-Iodine Gel Swabstick Non-Sterile
NDC: 59050-250 | Form: GEL
Manufacturer: Changzhou Maokang Medical Products Co. Ltd
Category: otc | Type: HUMAN OTC DRUG LABEL
Date: 20191202

ACTIVE INGREDIENTS: POVIDONE-IODINE 10 mg/1 g
INACTIVE INGREDIENTS: ANHYDROUS CITRIC ACID; WATER; NONOXYNOL-10; SODIUM HYDROXIDE; HYDROXYETHYL CELLULOSE (5000 MPA.S AT 1%); POTASSIUM IODIDE; GLYCERIN

MK Povidone- Iodine Gel Swabstick Non-Sterile

Active Ingredient

Povidone-Iodine USP 10%

Purpose

Antiseptic

Use

Antiseptic skin preparation

Warnings

Do not use

- if allergic to Iodine
- in the eyes

Stop use and ask a doctor if

- rednes, irritation, swelling or pain persists or increases
- infection occurs

Keep out of reach of children

In case of accidental ingestion, seek professional assistance or consult a poison control center immediately.

Avoid pooling beneath the patient

Ask a doctor before use if injuries are

- deep puncture wounds
- serious burns

Directions

apply product to skin as needed

Other Information

- 1% titratable
- for hospital or professional use only

Inactive Ingredients

Citric Acid, Alkyl Glucoside, Hydroxyethyl Cellulose, Nonoxynol-10, Glycerin, Sodium Hydroxide, Potassium Iodide, Purified Water